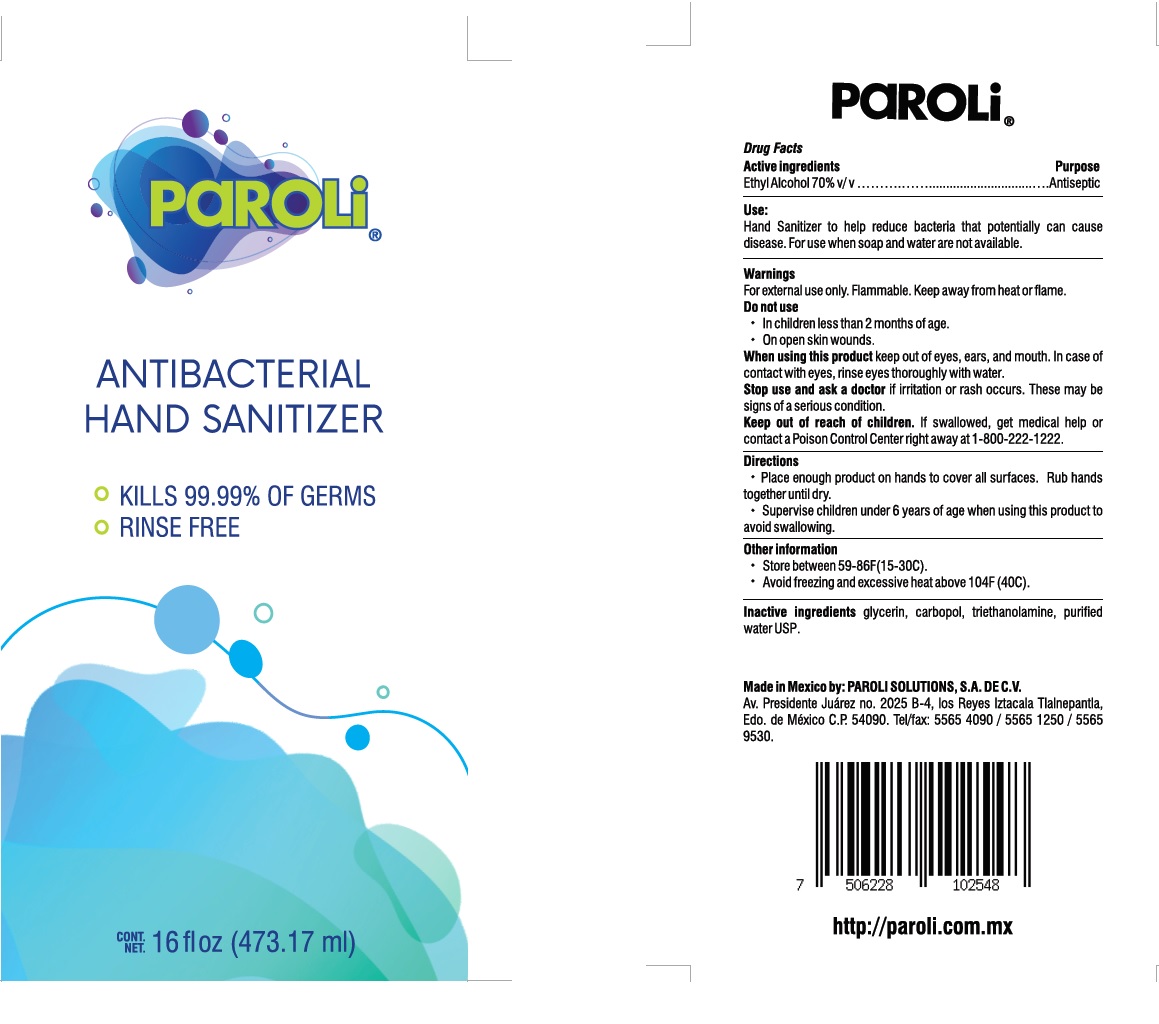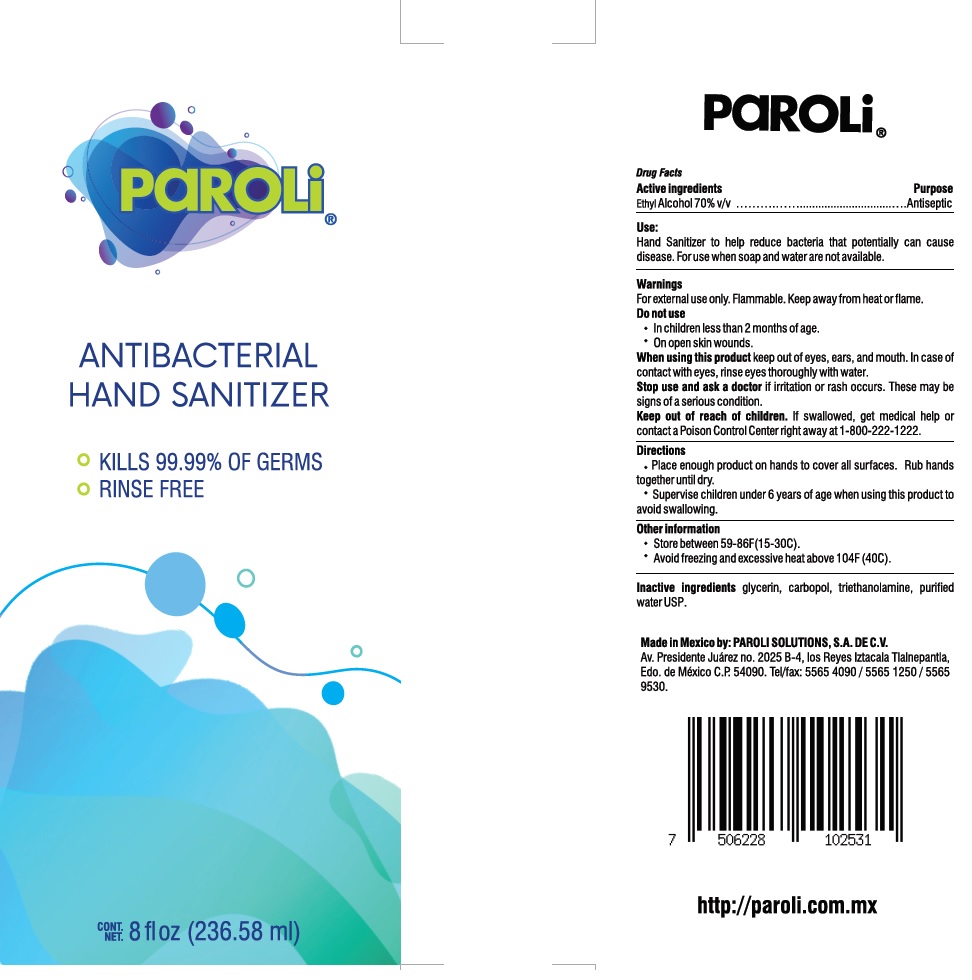 DRUG LABEL: Paroli Antibacterial Hand Sanitizer
NDC: 81161-004 | Form: GEL
Manufacturer: Paroli Solutions, S.A. de C.V.
Category: otc | Type: HUMAN OTC DRUG LABEL
Date: 20201201

ACTIVE INGREDIENTS: ALCOHOL 0.7 mL/1 mL
INACTIVE INGREDIENTS: GLYCERIN; CARBOMER HOMOPOLYMER, UNSPECIFIED TYPE; TROLAMINE

Paroli Antibacterial Hand Sanitizer

Active Ingredients

Ethyl alcohol 70% v/v

Purpose

Antiseptic

Use:

Hand Santizer to help reduce bacteria that potenially can cause disease. For use when soap and water are not available.

Warnings

For external use only. Flammable. Keep away from fire or flame.

Do not use

- In children less than 2 months of age.
- On open skin wounds.

When using this product

keep out of eyes, ears, and mouth. In case of contact with eyes, rinse eyes thoroughly with water.

Stop use and ask a doctor

if irritation or rash occurs. These may be signs of a serious condition.

Keep out of reach of children.

If swallowed, get medical help or contact a Poison Control Center right away at 1-800-222-1222.

Directions

- Place enough product on hands to cover all surfaces. Rub hands together until dry.
- Supervise children under 6 years of age when using this product to avoid swallowing.

Other information

- Store between 59-86F(15-30C).
- Avoid freezing and excessive heat above 104F (40C).

Inactive ingredients

glycerin, carbopol, triethanolamine, puified water USP.